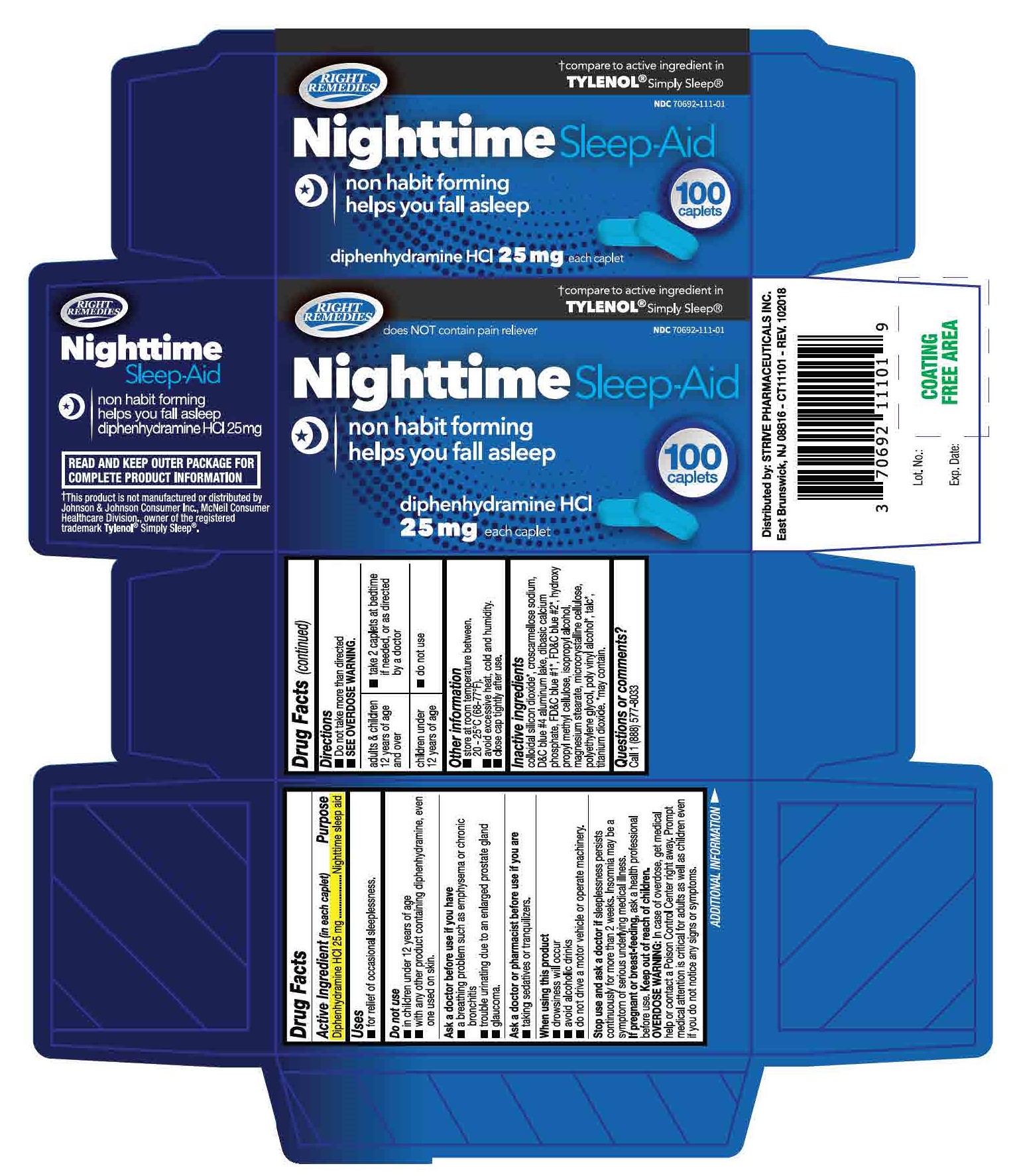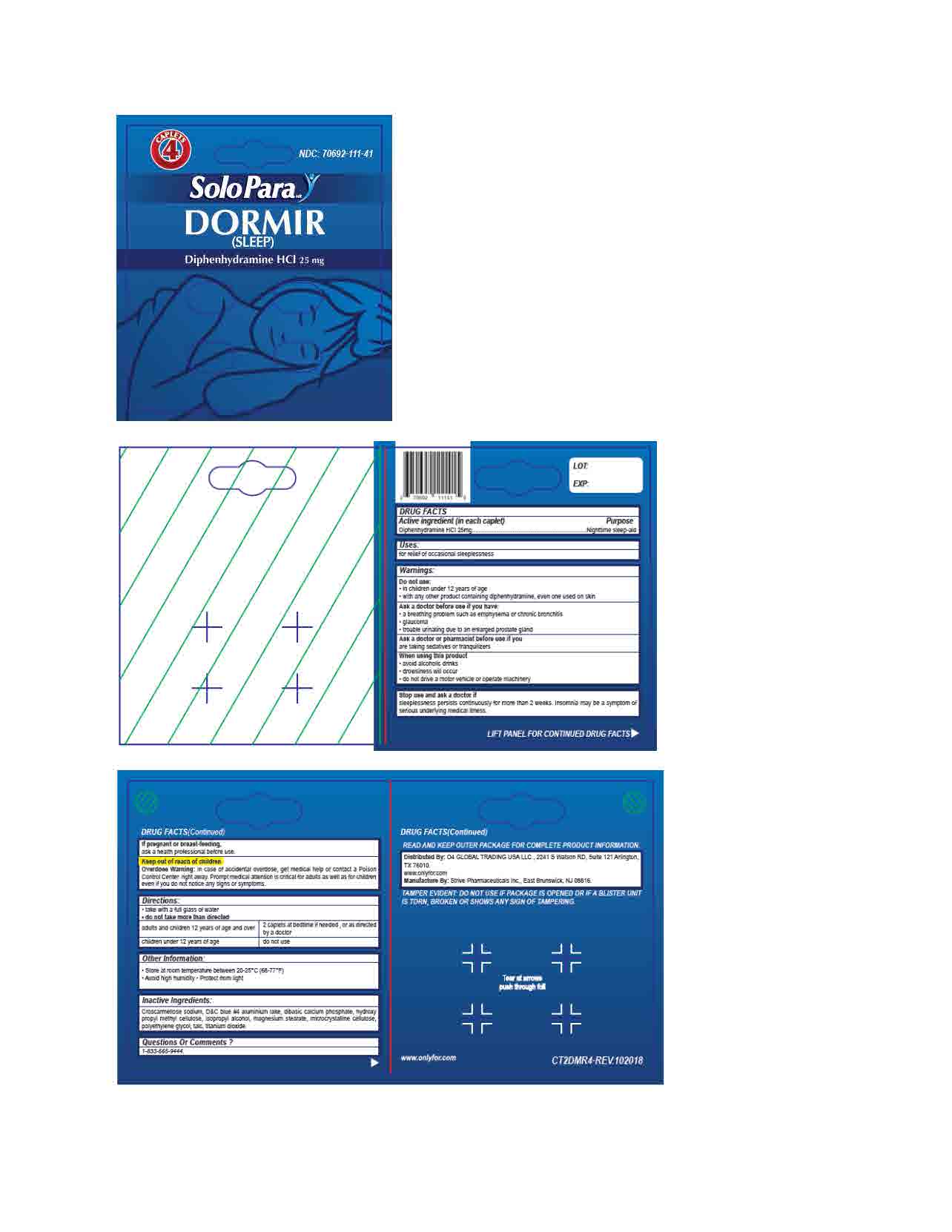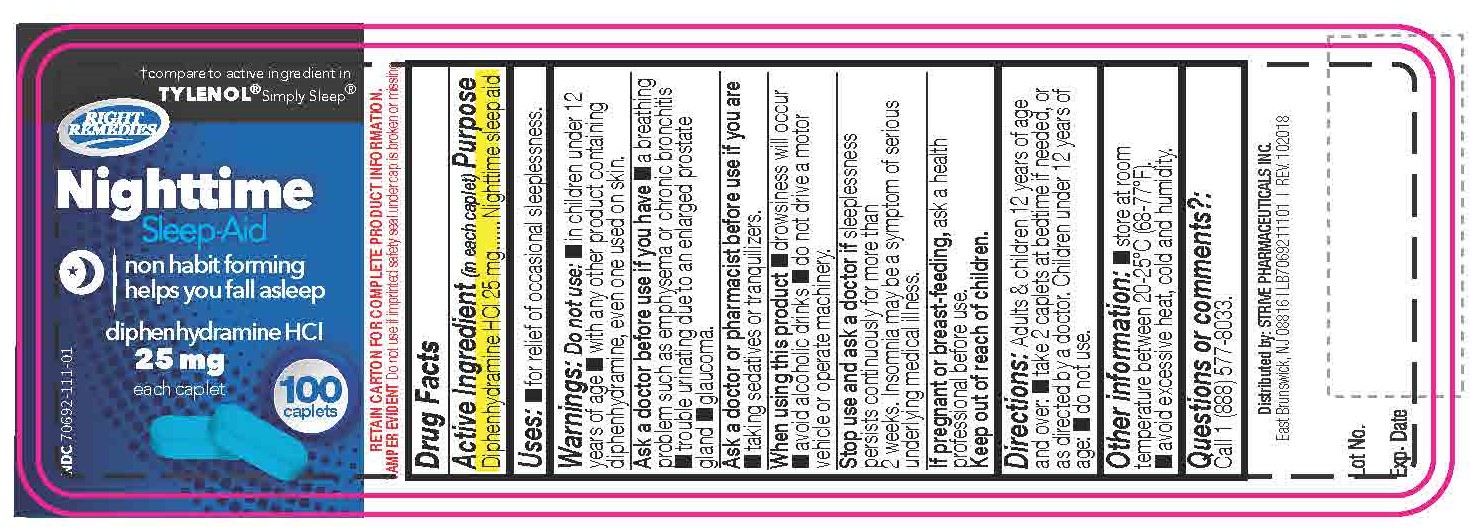 DRUG LABEL: Diphenhydramine Hydrochloride 25mg
NDC: 70692-111 | Form: TABLET
Manufacturer: Strive Pharmaceuticals Inc
Category: otc | Type: HUMAN OTC DRUG LABEL
Date: 20201116

ACTIVE INGREDIENTS: DIPHENHYDRAMINE HYDROCHLORIDE 25 mg/1 1
INACTIVE INGREDIENTS: D&C BLUE NO. 4; HYPROMELLOSES; ISOPROPYL ALCOHOL; MAGNESIUM STEARATE; MICROCRYSTALLINE CELLULOSE; POLYETHYLENE GLYCOL 400; TITANIUM DIOXIDE; CROSCARMELLOSE SODIUM; TALC; DIBASIC CALCIUM PHOSPHATE DIHYDRATE

Nighttime Sleep-Aid
Sleep - Dormir
(Diphenhydramine HCl 25mg) - Blue caplet

ACTIVE INGREDIENT

Diphenhydramine HCl 25mg

INACTIVE INGREDIENT

croscarmellose sodium, D&C blue #4 aluminium lake, dibasic calcium phosphate, hydroxy propyl methyl cellulose, isopropyl alcohol, magnesium stearate, microcrystalline cellulose, polyethyl;ene glycol, talc, titanium dioxide

DOSAGE AND ADMINISTRATION

- take with a full glass of water
- do not take more than directed

adults and children 12 years of age and over | 2 caplets at bedtime if needed, or as directed by a doctor
children under 12 years of age | do not use

INDICATIONS AND USAGE

for relief of occasional sleeplessness

Do not use

- in children under 12 years of age
- with any other product containing diphenhydramine, even one used on skin

Ask a doctor before use if you have

- a breathing problem such as emphysema or chronic bronchitis
- glaucoma
- trouble urinating due to an enlarged prostrate gland

Ask a doctor or a pharmacist before use if

you are taking sedatives or tranquilzers

When using this product

- avoid alcoholic drinks
- drowsiness will occur
- do not drive a motor vehicle or operate machinery

Stop use and ask a doctor if

sleeplessness persists continuously for more than 2 weeks. Insomnia may be a symptom of serious underlying medical illness

If pregnant or breast-feeding,

ask a health professional before use

Keep out of reach of children

Overdose warning: In case of accidental overdose, get medical help or contact a Poison Control Center right away. Prompt medical attention is critical for adults as well as for children even if you do not notice any signs or symptoms.

Keep out of reach of children

Overdose Warning: In case of accidental overdose, get medical help or contact a Poison Control Center right away. Prompt medical attention is critical for adults as well as for children even if you do not notice any signs or symptoms.

PURPOSE

Nighttime sleep-aid

OTHER SAFETY INFORMATION

- store at room temperature between 20ºC - 25ºC (68ºF - 77ºF)
- avoid high humidity
- protect from light